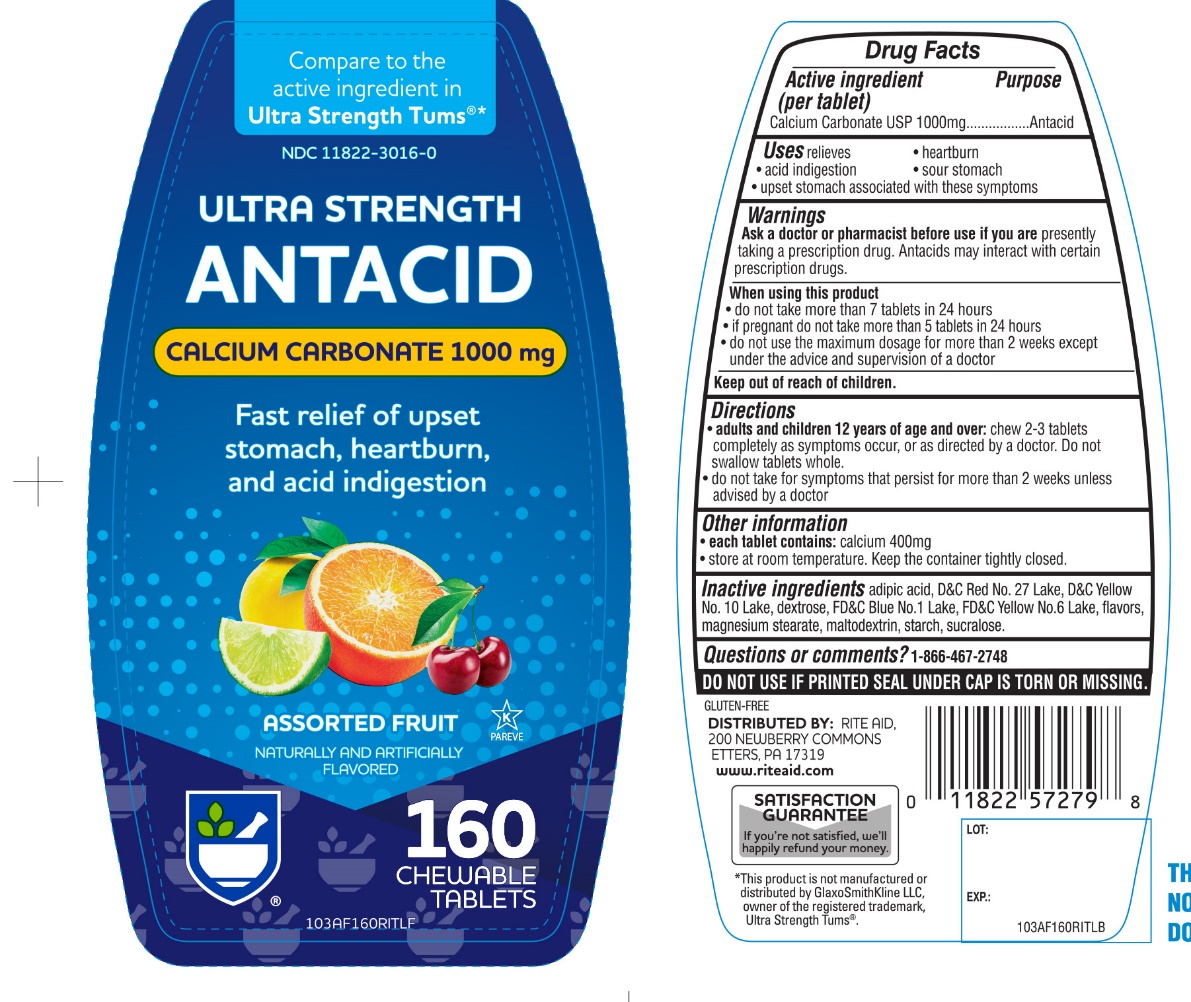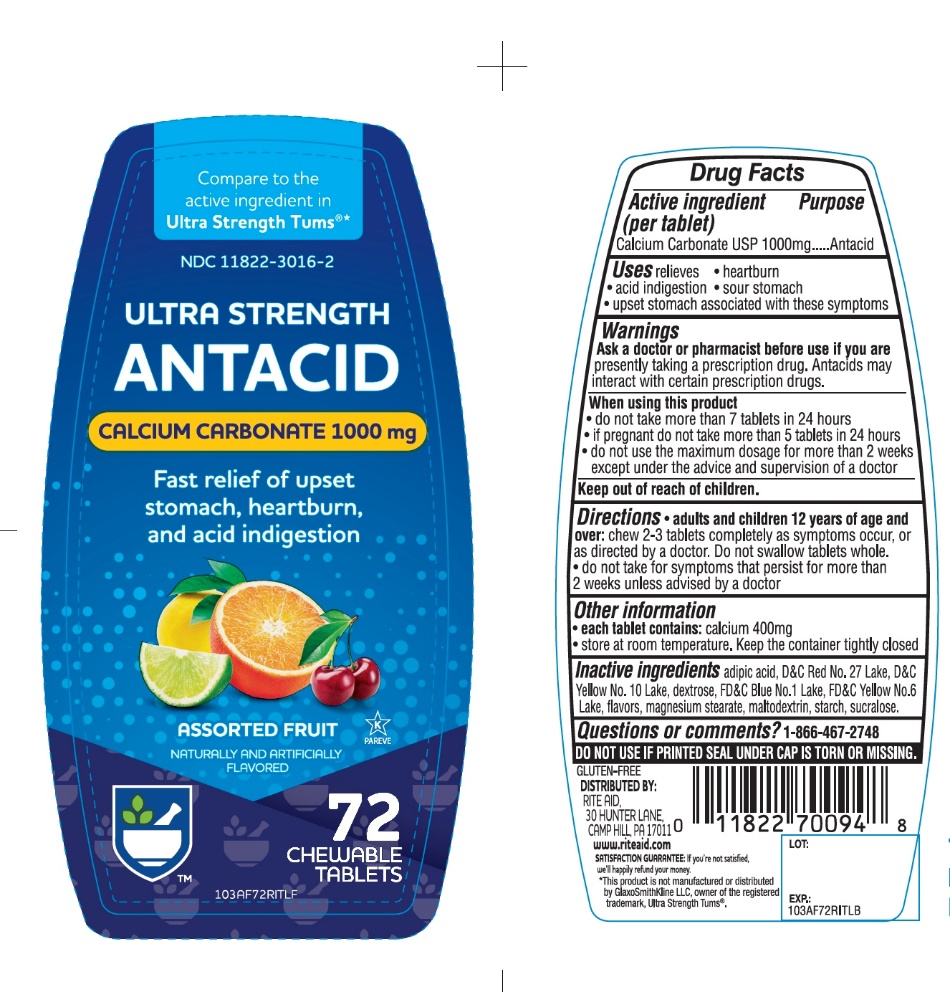 DRUG LABEL: RITE AID Pharmacy Ultra Strength
NDC: 11822-3016 | Form: TABLET, CHEWABLE
Manufacturer: RITE AID CORPORATION
Category: otc | Type: HUMAN OTC DRUG LABEL
Date: 20241030

ACTIVE INGREDIENTS: CALCIUM CARBONATE 1000 mg/1 1
INACTIVE INGREDIENTS: ADIPIC ACID; D&C RED NO. 27; D&C YELLOW NO. 10; DEXTROSE, UNSPECIFIED FORM; FD&C BLUE NO. 1; FD&C YELLOW NO. 6; MAGNESIUM STEARATE; MALTODEXTRIN; STARCH, CORN; SUCRALOSE

RITE AID Ultra Strength Assorted fruits Flavor Chewable Tablets

Active ingredient (per tablet)

Calcium Carbonate USP 1,000 mg

Purpose

Antacid

Uses

relieves

- heartburn
- sour stomach
- acid indigestion
- upset stomach associated with these symptoms

Warnings

Ask a doctor or pharmacist before use if you are presently taking a prescription drug. Antacids may interact with certain prescription drugs.

When using this product

- do not take more than 7 tablets in 24 hours
- if pregnant do not take more than 5 tablets in 24 hours
- do not use the maximum dosage for more than 2 weeks except under the advice and supervision of a doctor.

Directions

- adults and children 12 years of age and over: chew 2-3 tablets as symptoms occur, or as directed by a doctor. Do not swallow tablets whole.
- do not take for symptoms that persist for more than 2 weeks unless advised by a doctor

Other information

- each tablet contains: elemental calcium 400 mg
- store at room temperature. Keep the container tightly closed

Inactive ingredients

adipic acid, D&C Red No. 27, D&C Yellow No. 10, dextrose, FD&C Blue No. 1, FD&C Yellow No. 6, flavor, magnesium stearate, maltodextrin, starch, sucralose.

Questions or comments?

1-866-467-2748

SAFETY SEALED: DO NOT USE IF PRINTED SEAL UNDER CAP IS TORN OR MISSING

Package/Label Principal Display Panel

RITE AID® PHARMACY

Compare to the active ingredients Ultra Strength Tums®

ULTRA STRENGTH

Antacid

Calcium Carbonate 1000mg

fast relief of upset stomach, heartburn, and acid indigestion

Assorted Fruit Flavors

Naturally and artificially flavored

GLUTEN-FREE

DISTRIBUTED BY: RITE AID

30 HUNTER LANE, CAMP HILL, PA 17011

IF YOU’RE NOT SATISFIED, WE’LL HAPPILY REFUND YOUR MONEY.

*This product is not manufactured and distributed by GlaxoSmithKline LLC, owner of the registered trademark, Ultra Strength Tums®

Package Label for 160 Chewable Tablets